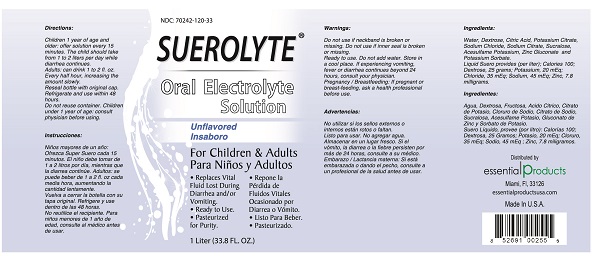 DRUG LABEL: SUEROLYTE Oral Electrolyte Solution Unflavored Flavor
NDC: 70242-120 | Form: LIQUID
Manufacturer: Dannso Corp./d.b.a. Essential Products
Category: other | Type: DIETARY SUPPLEMENT
Date: 20150814

ACTIVE INGREDIENTS: DEXTROSE MONOHYDRATE 25 g/1 L; POTASSIUM CITRATE 20 meq/1 L; SODIUM CHLORIDE 45 meq/1 L; SODIUM CHLORITE 35 meq/1 L; ZINC 35 meq/1 L
INACTIVE INGREDIENTS: Water; Citric Acid MONOHYDRATE ; Sodium Citrate, UNSPECIFIED FORM ; Sucralose; Acesulfame Potassium ; POTASSIUM SORBATE

SUEROLYTE Oral Electrolyte Solution Unflavored Flavor

STATEMENT OF IDENTITY

Dietary Supplement [This statement has not been evaluated by the Food and Drug Administration (FDA). This product is not intended to diagnose, treat, cure or prevent any disease.]

Warnings

Do not use if neckband is broken or missing. Do not use if inner seal is broken or missing.
Ready to use. Do not add water. Store in a cool place. If experirncing vomitting, fever, or diarrhea continues beyond 24 hours, consult your physician.
Pregnancy / Breastfeeding: If pregnant or breastfeeding, ask a health professional before use.

Directions

Children 1 year of age and older: offer solution every 15 minutes. The child should take from 1 to 2 liters per day while diarrhea continues.
Adults: can drink 1 to 2 fl. oz. every half hour, increasing the amount slowly. Reseal bottle with original cap.
Refrigerate and use within 48 hours.
Do not reuse container. Children under 1 year of age: consults physician before using.

Questions or Comments

Distributed by

Essential Products Miami FL 33126

www.essentialproductsuse.com

Made in U.S.A.